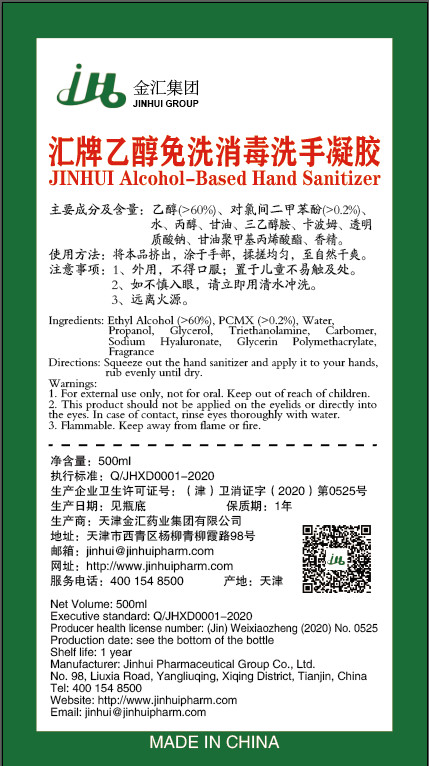 DRUG LABEL: JINHUI Alcohol-Based Hand Sanitizer
NDC: 65377-001 | Form: GEL
Manufacturer: Tianjin Jinhui Pharmaceutical Group Co., Ltd.
Category: otc | Type: HUMAN OTC DRUG LABEL
Date: 20200408

ACTIVE INGREDIENTS: ALCOHOL 300 mL/500 mL
INACTIVE INGREDIENTS: CARBOMER HOMOPOLYMER, UNSPECIFIED TYPE; WATER; PROPYL ALCOHOL; GLYCERIN; CHLOROXYLENOL; HYALURONATE SODIUM

DOSAGE AND ADMINISTRATION

Keep away from flame or fire.

INACTIVE INGREDIENT

PCMX

Water

Propanol

Glycerol

Triethanolamine

Carbomer

Sodium Hyaluronate

INDICATIONS AND USAGE

Squeeze out the hand sanitizer and apply it to your hands,rub evenly until dry.

ACTIVE INGREDIENT

Ethyl Alcohol

keep out of children

PURPOSE

Disinfection
Sterilization
No Rinseing

WARNINGS

1. For external use only, not for oral. Keep out of reach of children.
2. This product should not be applied on the cyelids or directly into the eyes. In case of contact, rinse eyes thoroughly with water.
3. Flammable. Keep away from flame or fire.